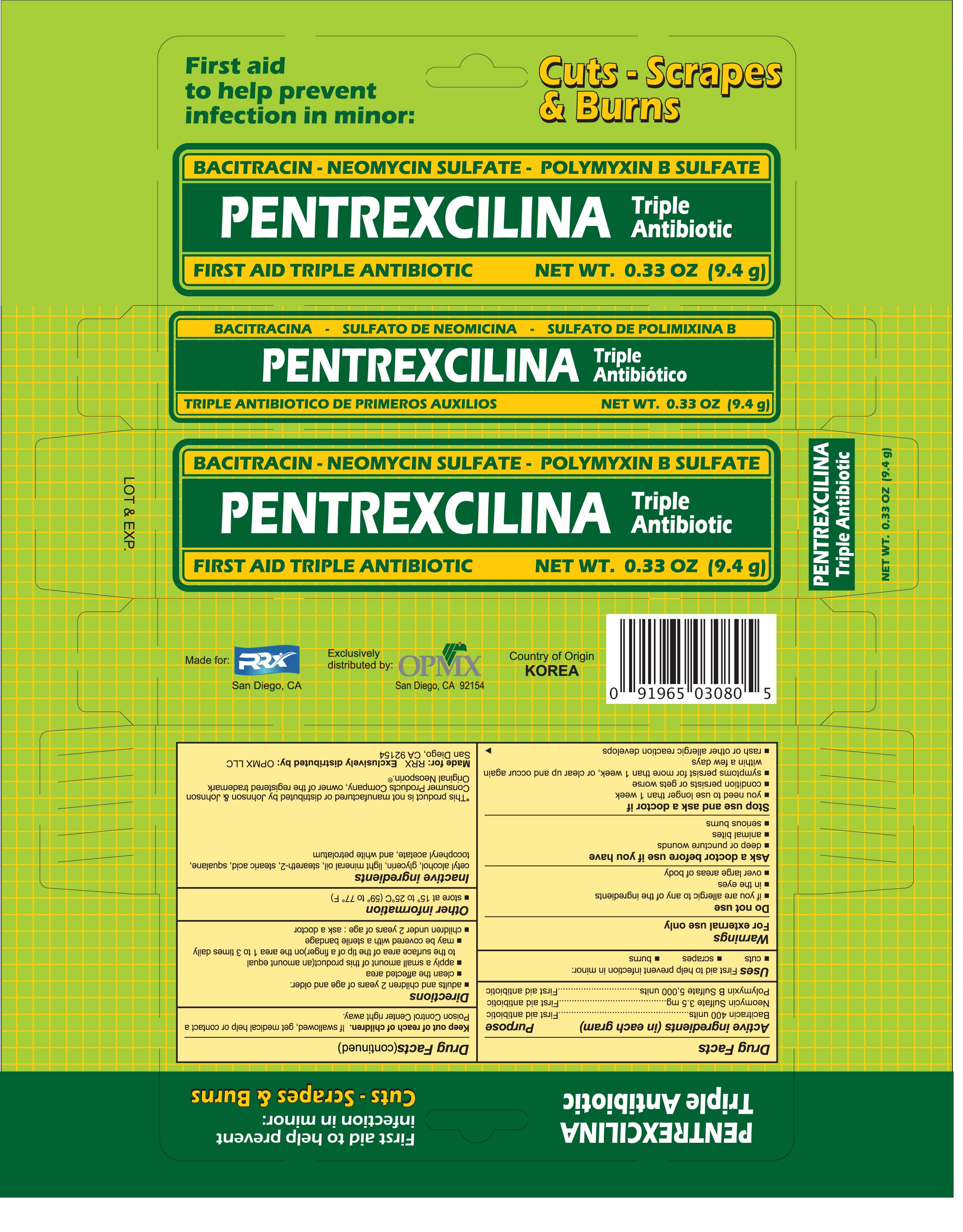 DRUG LABEL: Pentrexcilina Triple Antibiotic
NDC: 69729-080 | Form: OINTMENT
Manufacturer: OPMX LLC
Category: otc | Type: HUMAN OTC DRUG LABEL
Date: 20150921

ACTIVE INGREDIENTS: BACITRACIN ZINC 400 [USP'U]/1 g; NEOMYCIN SULFATE 3.5 mg/1 g; POLYMYXIN B SULFATE 5000 [USP'U]/1 g
INACTIVE INGREDIENTS: CETYL ALCOHOL; GLYCERIN; LIGHT MINERAL OIL; STEARETH-2; SQUALANE; STEARIC ACID; .ALPHA.-TOCOPHEROL ACETATE, D-; PETROLATUM

Drug Facts

Active ingredient

Bacitracin Zinc 400 units

Neomycin Sulfate 3.5mg

Polymyxin B Sulfate 5,000 units

Purpose

First aid antibiotic

First aid antibiotic

First aid antibiotic

Uses

First aid to help prevent infection in minor:

- cuts
- scrapes
- burns

Warnings

For external use only

Do not use

- if you are allergic to any of the ingredients
- in the eyes
- over large areas of body

Ask a doctor before use if you have

- deep or puncture wounds
- animal bites
- serious burns

Keep out of reach of children.

If swallowed, get medical help or contact a Poison Control Center right away.

Directions

- adults and children 2 years of age or older:
  - clean the affected area
  - apply a small amount of this product (an amount equal tot the surface area of the tip of a finer) on the area 1 to 3 times daily
  - may be covered with a sterile bandage
- children under 2 years of age: ask a doctor

Other information

- store at 15° - 25° C (59° to 77°F)

Inactive ingredients

Cetyl alcohol, Glycerin, Light mineral oil, Squalane, Steareth-2, Stearic acid, Tocopheryl acetate, dand White petrolatum

Package label panel

Pentrexcilina Triple Antibiotic